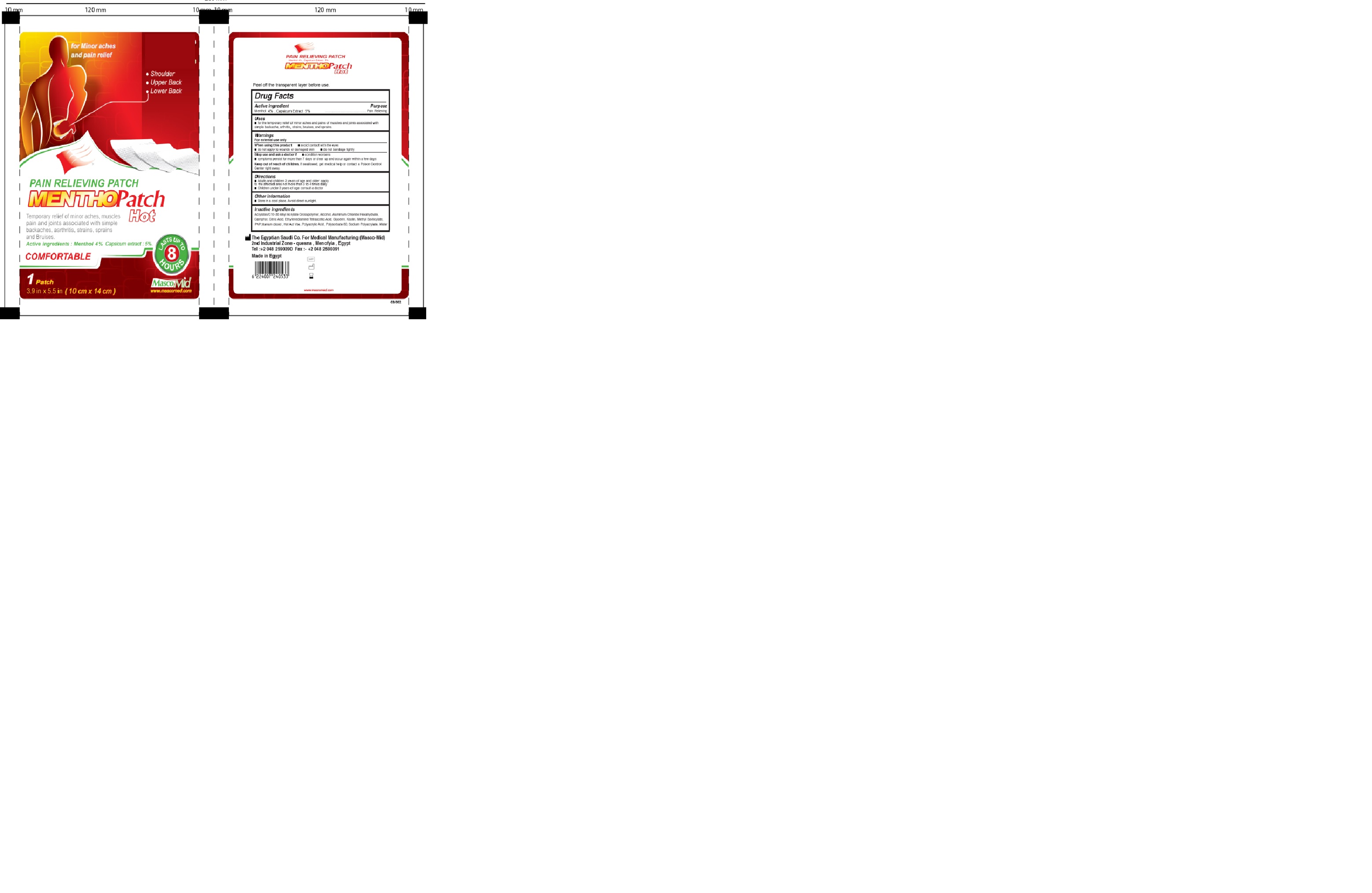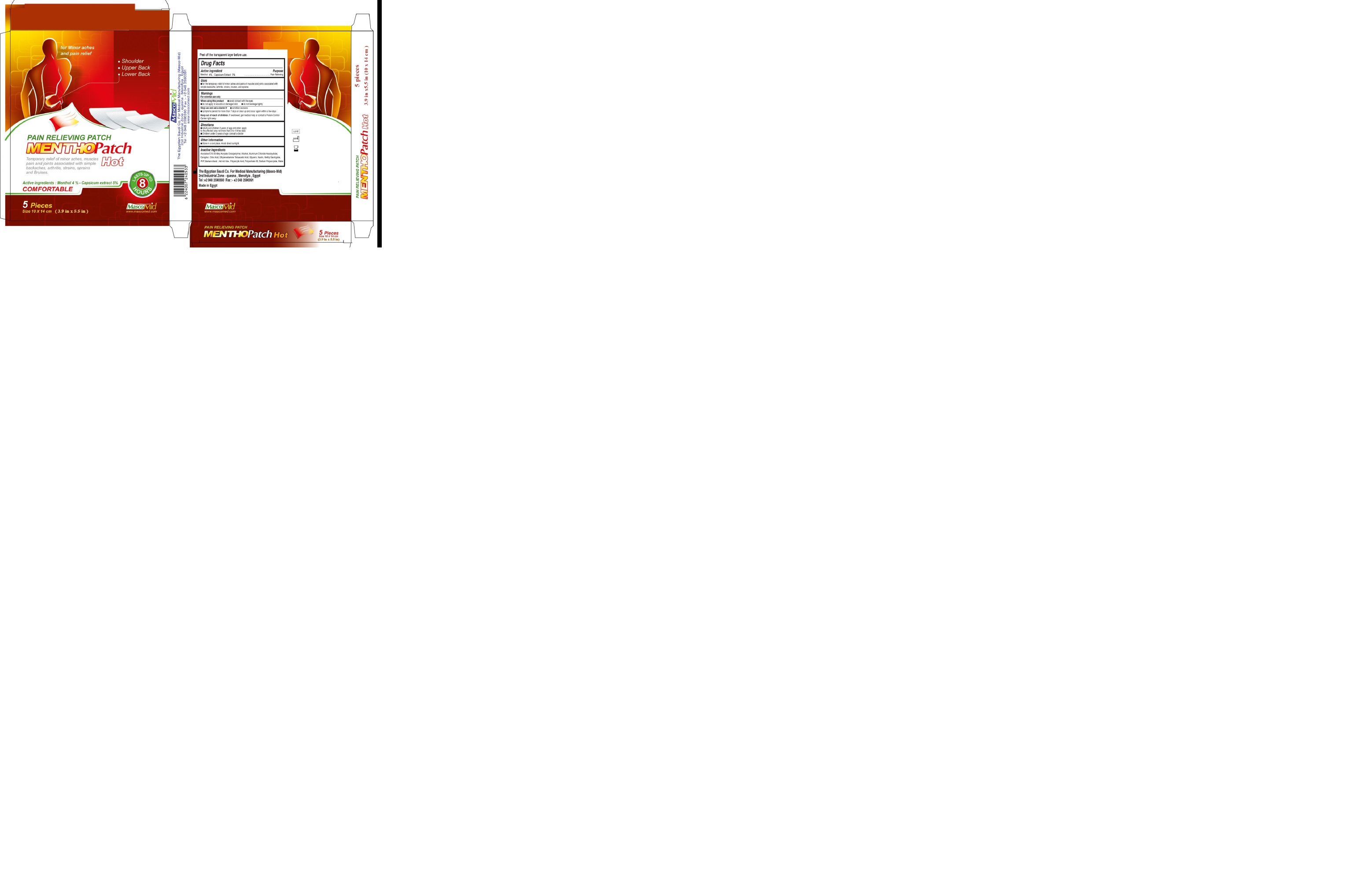 DRUG LABEL: Menthopatch
NDC: 72602-004 | Form: PATCH
Manufacturer: THE EGYPTIAN SAUDI CO FOR MEDICAL MANUFACTURING MASCOMID
Category: otc | Type: HUMAN OTC DRUG LABEL
Date: 20251006

ACTIVE INGREDIENTS: CAPSICUM 50 mg/1 1; MENTHOL 40 mg/1 1
INACTIVE INGREDIENTS: GLYCERIN; SODIUM POLYACRYLATE (2500000 MW); ALUMINUM CHLORIDE ANHYDROUS; CITRIC ACID MONOHYDRATE; TARTARIC ACID; POLYSORBATE 80; ISOPROPYL MYRISTATE; CARBOXYMETHYLCELLULOSE SODIUM (0.9 CARBOXYMETHYL SUBSTITUTION PER SACCHARIDE; 600 MPA.S AT 2%); EDETATE DISODIUM; POLYACRYLIC ACID (800000 MW); WATER; TITANIUM DIOXIDE; METHYL SALICYLATE; CAMPHOR (NATURAL); CARBOMER COPOLYMER TYPE B (ALLYL PENTAERYTHRITOL CROSSLINKED)

MenthoPatch Hot

Active Ingrdient

Menthol 4%

Capsicum Extract 5 %

Purpose

Temporarily relieves minor pain.

Warnings

- For external use only
- When using this product
- Avoid contact with the eyes
- Do not apply to wounds, or to damaged skin
- Do not bandage tightly.
- Consult doctor if pain continued after 7 days using product or excess skin inflamation.
- Children under 12 years of age: consult doctor.

Direction

- Clean and dry the affected area.
- Open the cover of product and peel of the transparent layer of the product.
- Paste the product on affected area.
- Menthol patch is effective up to 8 hours which can replaced as needed.

DOSAGE & ADMINISTRATION

- use menthol patch from 2 to 3 days

Stop use and ask doctor

- If condition worsens
- If symptoms persist more than 7 days or clear up and occur again with a few days

Storage

- Store in cool dry place avoid direct sunlight.

Keep out of reach of children

If swallowed, get medical help or contact a Poison Control Center right away

Inactive ingredients

Glycerin 24

Sodium poly acryl ate 8
Aluminum chloride hexahydrate
Citric acid
Tartaric acid
Polysorbate 80
Isopropyl myristate alcohol 2.5
Car boxy methyl cellulose
EDETA .2Na 0.5
Polyvinyl pyrolidone(PVP-K90)
Water 48
Titanium dioxide
Methyl salicylate
Camphor
Hot act vbe 0.2
ACRYLATE/ C10-30 ALKYL ACRYLATE cross polymer